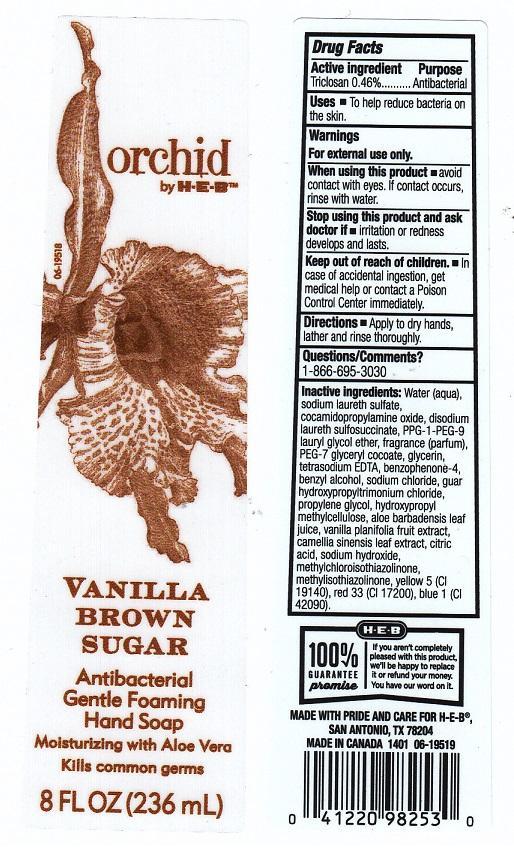 DRUG LABEL: ORCHID BY H E B
NDC: 37808-107 | Form: LIQUID
Manufacturer: H E B
Category: otc | Type: HUMAN OTC DRUG LABEL
Date: 20140304

ACTIVE INGREDIENTS: TRICLOSAN 4.6 mg/1 mL
INACTIVE INGREDIENTS: WATER; SODIUM LAURETH SULFATE; COCAMIDOPROPYLAMINE OXIDE; DISODIUM LAURETH SULFOSUCCINATE; PPG-1-PEG-9 LAURYL GLYCOL ETHER; PEG-7 GLYCERYL COCOATE; GLYCERIN; EDETATE SODIUM; SULIBENZONE; BENZYL ALCOHOL; SODIUM CHLORIDE; GUAR HYDROXYPROPYLTRIMONIUM CHLORIDE (1.7 SUBSTITUENTS PER SACCHARIDE); PROPYLENE GLYCOL; HYPROMELLOSES; ALOE VERA LEAF; VANILLA; GREEN TEA LEAF; CITRIC ACID MONOHYDRATE; SODIUM HYDROXIDE; METHYLCHLOROISOTHIAZOLINONE; METHYLISOTHIAZOLINONE; FD&C YELLOW NO. 5; D&C RED NO. 33; FD&C BLUE NO. 1

DRUG FACTS

ACTIVE INGREDIENT

TRICLOSAN 0.46%

PURPOSE

ANTIBACTERIAL

USES

TO HELP REDUCE BACTERIA ON THE SKIN

WARNINGS

FOR EXTERNAL USE ONLY

WHEN USING THIS PRODUCT

AVOID CONTACT WITH EYES. IF CONTACT OCCURS, RINSE WITH WATER

STOP USING THIS PRODUCT AND ASK DOCTOR IF

IRRITATION OR REDNESS DEVELOPS AND LASTS

KEEP OUT OF REACH OF CHILDREN

IN CASE OF ACCIDENTAL INGESTION, GET MEDICAL HELP OR CONTACT A POISON CONTROL CENTER IMMEDIATELY

DIRECTIONS

APPLY TO DRY HANDS, LATHER AND RINSE THOROUGHLY

QUESTIONS/COMMENTS?

1-866-695-3030

INACTIVE INGREDIENTS

WATER (AQUA), SODIUM LAURETH SULFATE, COCAMIDOPROPYLAMINE OXIDE, DISODIUM LAURETH SULFOSUCCINATE, PPG-1-PEG-9 LAURYL GLYCOL ETHER, FRAGRANCE (PARFUM), PEG-7 GLYCERYL COCOATE, GLYCERIN, TETRASODIUM EDTA, BENZOPHENONE-4, BENZYL ALCOHOL, SODIUM CHLORIDE, GUAR HYDROXYPROPYLTRIMONIUM CHLORIDE, PROPYLENE GLYCOL, HYDROXYPROPYL METHYLCELLULOSE, ALOE BARBADENSIS LEAF JUICE, VANILLA PLANIFOLIA FRUIT EXTRACT, CAMELLIA SINENSIS LEAF EXTRACT, CITRIC ACID, SODIUM HYDROXIDE, METHYLCHLOROISOTHIAZOLINONE, METHYLISOTHIAZOLINONE, YELLOW 5 (CI 19140), RED 33 (CI 17200), BLUE 1 (CI 42090)